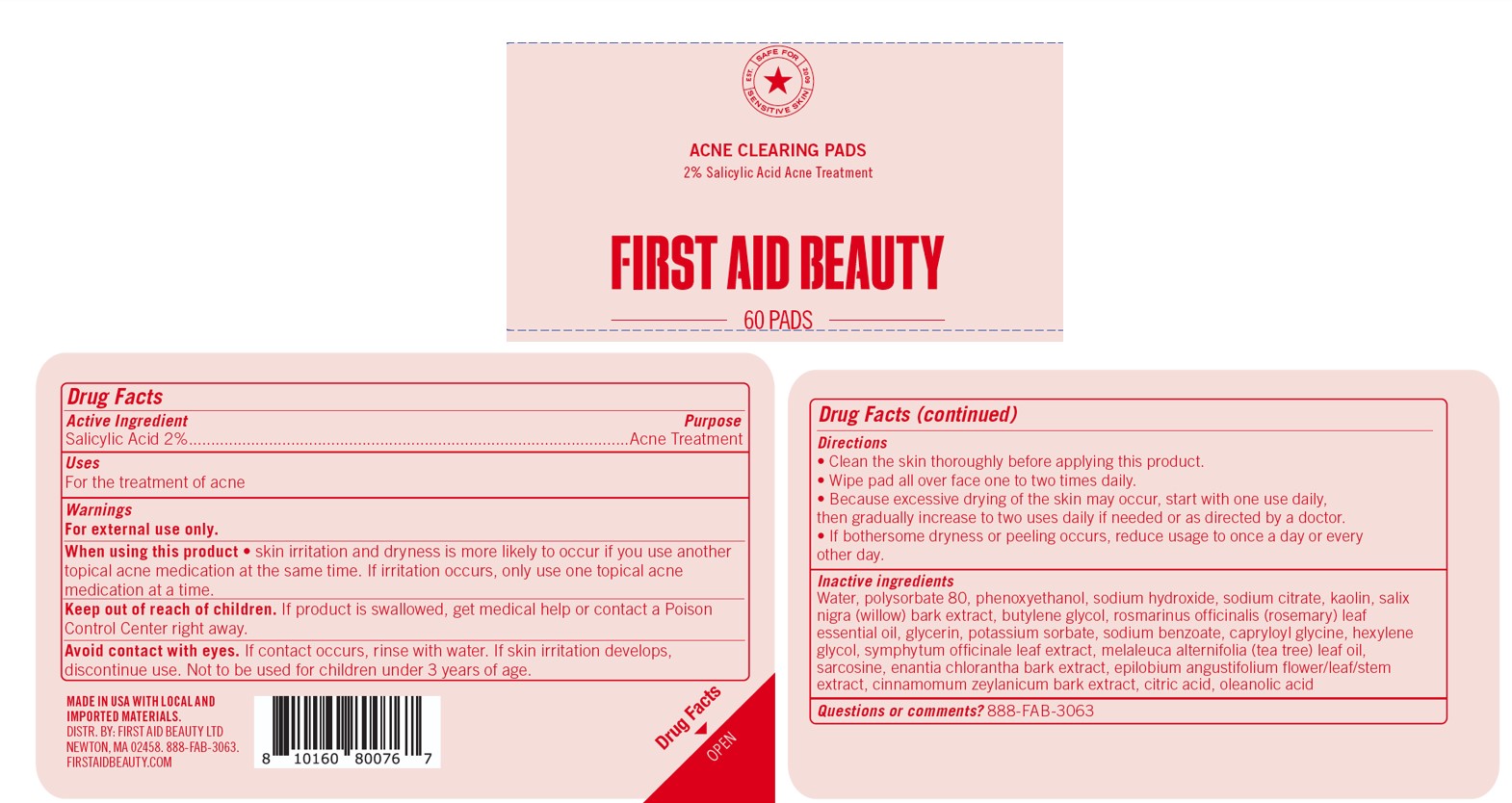 DRUG LABEL: First Aid Beauty Acne Clearing Pads
NDC: 84126-119 | Form: DISC
Manufacturer: The Procter & Gamble Manufacturing Company
Category: otc | Type: HUMAN OTC DRUG LABEL
Date: 20250522

ACTIVE INGREDIENTS: SALICYLIC ACID 2 g/100 mL
INACTIVE INGREDIENTS: CITRIC ACID; CAPRYLOYL GLYCINE; ROSEMARY OIL; EPILOBIUM ANGUSTIFOLIUM FLOWERING TOP; CINNAMON BARK OIL; OLEANOLIC ACID; TEA TREE OIL; KAOLIN; HEXYLENE GLYCOL; ANNICKIA CHLORANTHA BARK; SODIUM HYDROXIDE; COMFREY LEAF; SODIUM CITRATE; BUTYLENE GLYCOL; PHENOXYETHANOL; POLYSORBATE 80; WATER; GLYCERIN; POTASSIUM SORBATE; SODIUM BENZOATE; SARCOSINE; SALIX NIGRA BARK

First Aid Beauty Acne Clearing Pads

Drug Facts

Active ingredients

Salicylic Acid 2%

Purpose

Acne Treatment

Uses

- for the treatment of acne

Warnings

For external use only.

WHEN USING

Skin irritation and dryness is more likely to occur if you use another topical acne medication at the same time.

If irritation occurs, only use one topical acne medication at a time.

Avoid contact with eyes. If contact occurs, rinse eyes thoroughly with water.

Keep out of reach of children. If swallowed, get medical help or contact a Poison Control Center right away.

Directions

• Clean the skin thoroughly before applying this product.
• Wipe pad all over face one to two times daily.
• Because excessive drying of the skin may occur, start with one use daily,
then gradually increase to two uses daily if needed or as directed by a doctor.
• If bothersome dryness or peeling occurs, reduce usage to once a day or every
other day.

INACTIVE INGREDIENT

Water, polysorbate 80, phenoxyethanol, sodium hydroxide, sodium citrate, kaolin, salix nigra (willow) bark extract, butylene glycol, rosmarinus officinalis (rosemary) leaf essential oil, glycerin, potassium sorbate, sodium benzoate, capryloyl glycine, hexylene glycol, symphytum officinale leaf extract, melaleuca alternifolia (tea tree) leaf oil, sarcosine, enantia chlorantha bark extract, epilobium angustifolium flower/leaf/stem extract, cinnamomum zeylanicum bark extract, citric acid, oleanolic acid

Questions:

888-FAB-3063

MADE IN USA

FIRST AID BEAUTY LTD

NEWTON, MA 02458

WWW.FIRSTAIDBEAUTY.COM

PRINCIPAL DISPLAY PANEL - 60 pads carton

First Aid Beauty

ACNE CLEARING PADS

2% Salicylic Acid Treament

Safe for sensitive skin

60 PADS